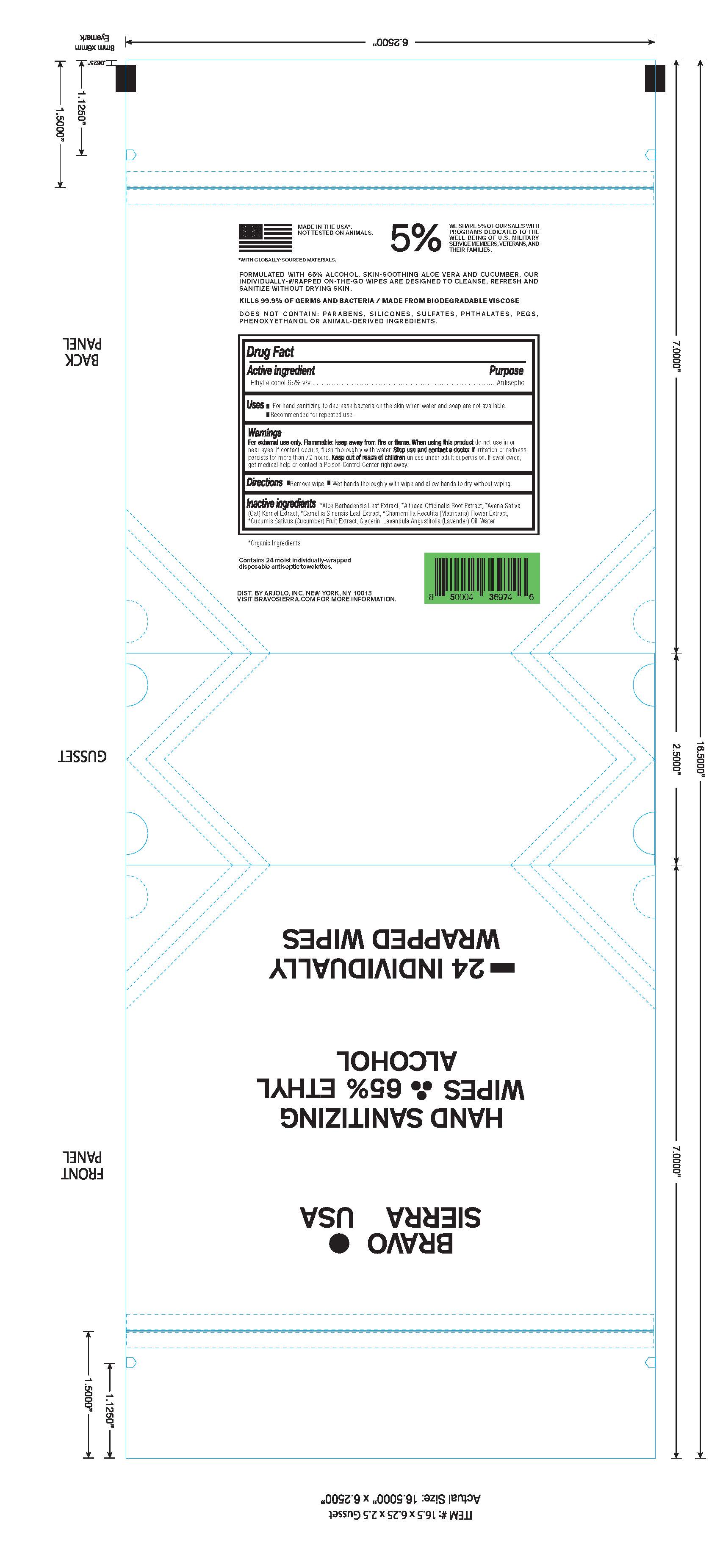 DRUG LABEL: Bravo Sierra USA Hand Sanitizing Wipes 65% Ethyl Alcohol
NDC: 73206-040 | Form: SWAB
Manufacturer: ARJOLO, INC.
Category: otc | Type: HUMAN OTC DRUG LABEL
Date: 20201110

ACTIVE INGREDIENTS: ALCOHOL 65 mL/100 mL
INACTIVE INGREDIENTS: ALOE VERA LEAF; ALTHAEA OFFICINALIS ROOT; CAMELLIA SINENSIS FLOWER; AVENA SATIVA LEAF; CAMELLIA RETICULATA SEED OIL; CUCUMIS SATIVUS LEAF; GLYCERIN; WATER; LAVANDULA ANGUSTIFOLIA FLOWER

DRUG FACTS

Active Ingredient(s)

Ethyl Alcohol 65%

Purpose

Antiseptic

Use

• For hand sanitizing to decrease bacteria on the skin when water and soap are not available. • Recommened for repeated use.

Warnings

For external use only. Flammable. Keep away from heat or flame

Do not use

- in children less than 2 months of age
- on open skin wounds

When using this product do not use in or near the eyes. In case of contact, rinse eyes thoroughly with water.

Stop Use and ask doctor if irritation or redness persisits for more than 72 hours.

Keep out of reach of children unless under adult supervision. If swallowed, get medical help or contact a Poison Control Center right away.

Directions

- Remove wipe. • Wet hands thoroughly with wipe and allow hands to dry without wiping.

Inactive ingredients

Aloe Barbadensis Leaf Juice, Althaea Officinalis Root Extract, Camellia Sinensis Leaf Extract, Avena Sativa (Oat) Kernel Extract, Chamomilla Recutita (Matricaria) Flower Extract, Cucumis Sativus (Cucumber) Fruit Extract, Glycerin, Lavendula Angustifolia (Lavender) Oil, Water.